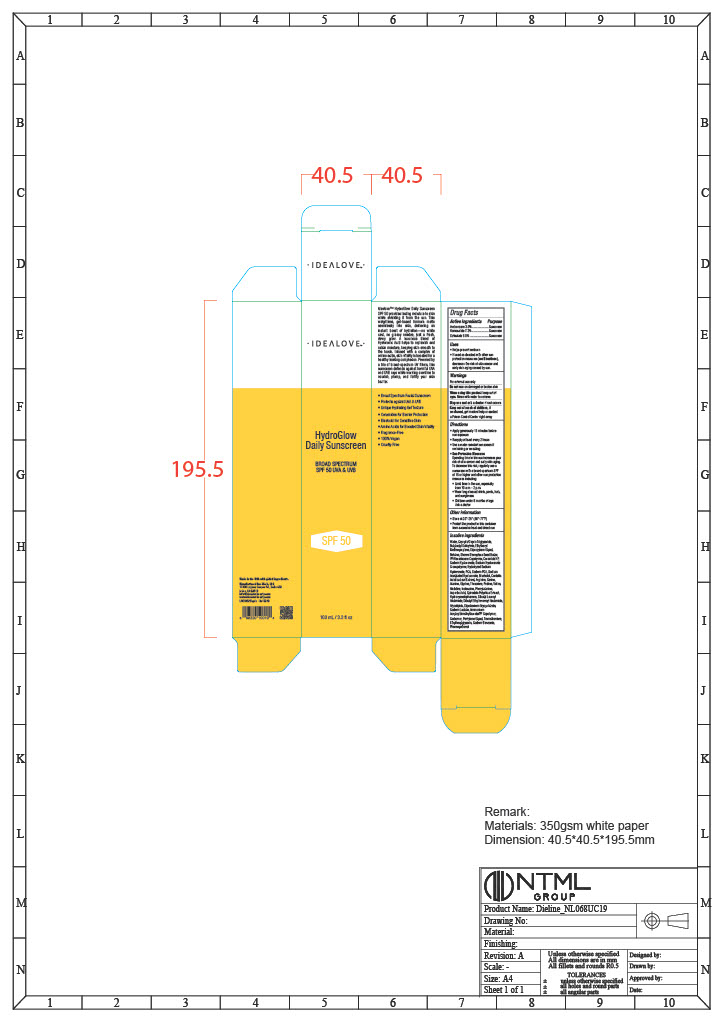 DRUG LABEL: HydroGlow Daily Sunscreen BROAD SPECTRUM SPF 50 UVA and UVB
NDC: 82287-0002 | Form: LOTION
Manufacturer: IHerb, LLC
Category: otc | Type: HUMAN OTC DRUG LABEL
Date: 20251001

ACTIVE INGREDIENTS: AVOBENZONE 3 mg/100 mL; OCTISALATE 5 mg/100 mL; HOMOSALATE 7.3 mg/100 mL
INACTIVE INGREDIENTS: PSEUDOMONAS GLUCOSE FERMENTATION RHAMNOLIPIDS; BUTYLOCTYL SALICYLATE; CAPRYLIC/CAPRIC TRIGLYCERIDE; ETHYLHEXYL METHOXYCRYLENE; BETAINE; SHOREA STENOPTERA SEED BUTTER; VP/HEXADECENE COPOLYMER; BISABOLOL; HYDROXYACETOPHENONE; PENTYLENE GLYCOL; SODIUM PCA; SPIRODELA POLYRHIZA; ISOLEUCINE; THREONINE; PHENYLALANINE; SODIUM ACETYLATED HYALURONATE; CERAMIDE NP; ARGININE; VALINE; SODIUM BENZOATE; PHENOXYETHANOL; DIBUTYL LAUROYL GLUTAMIDE; SODIUM LACTATE; PROLINE; AMMONIUM ACRYLOYLDIMETHYLTAURATE/VP COPOLYMER; ASPARTIC ACID; DIBUTYL ETHYLHEXANOYL GLUTAMIDE; ALANINE; CARBOMER; DIPROPYLENE GLYCOL; CENTELLA ASIATICA LEAF; SODIUM HYALURONATE; SERINE; GLYCINE; TROMETHAMINE; DIPOTASSIUM GLYCYRRHIZATE; ETHYLHEXYLGLYCERIN; PCA; HISTIDINE; WATER

HEALTH CLAIM

Idealove™ HydroGlow Daily Sunscreen SPF 50 provides lasting moisture to skin while shielding it from the sun. This weightless, gel-based formula melts seamlessly into skin, delivering an instant boost of hydration—no white cast, no greasy residue, just a fresh, dewy glow. A luxurious blend of Hyaluronic Acid helps to replenish and retain moisture, keeping skin smooth to the touch.

Infused with a complex of amino acids, skin vitality is boosted for a healthy-looking complexion. Powered by a trio of broad-spectrum UV filters, this sunscreen defends against harmful UVA and UVB rays while working overtime to nourish, plump, and fortify your skin barrier.

• Broad Spectrum Facial Sunscreen

• Protects against UVA & UVB

• Unique Hydrating Gel Texture

• Ceramides for Barrier Protection

• Bisabolol for Sensitive Skin

• Amino Acids for Boosted Skin Vitality

• Fragrance-Free

• 100% Vegan

• Cruelty-Free

DESCRIPTION

Made in the USA with global ingredients. Manufactured for: iHerb, LLC 17400 Laguna Canyon Rd., Suite 400 Irvine, CA 92618 info@idealovebeauty.com www.idealovebeauty.com LREV0525hgds ide10019

Active Ingredients Purpose

Avobenzone 3.0%....................Sunscreen

Homosalate 7.3%.....................Sunscreen

Octisalate 5.0%........................Sunscreen

Uses

• Helps prevent sunburn • If used as directed with other sun, protection measures (see Directions), decreases the risk of skin cancer and early skin aging caused by sun.

Do not use on damaged or broken skin

Keep out of reach of children, if swallowed, get medical help or contact a Poison Control Center right away

When using this product keep out of eyes. Rinse with water to remove.

Stop use and ask a doctor if rash occurs.

Other information

• Store at 20°-25° (68°-77°F)

• Protect the product in this container from excessive heat and direct sun

Inactive ingredients

Water, Caprylic/Capric Triglyceride, Butyloctyl Salicylate, Ethylhexyl Methoxycrylene, Dipropylene Glycol, Betaine, Shorea Stenoptera Seed Butter, VP/Hexadecene Copolymer, Ceramide NP, Sodium Hyaluronate, Sodium Hyaluronate Crosspolymer, Hydrolyzed Sodium Hyaluronate, PCA, Sodium PCA, Sodium Acetylated Hyaluronate, Bisabolol, Centella Asiatica Leaf Extract, Arginine, Serine, Alanine, Glycine, Threonine, Proline, Valine, Histidine, Isoleucine, Phenylalanine, Aspartic Acid, Spirodela Polyrhiza Extract, Hydroxyacetophenone, Dibutyl Lauroyl Glutamide, Dibutyl Ethylhexanoyl Glutamide, Glycolipids, Dipotassium Glycyrrhizate, Sodium Lactate, Ammonium Acryloyldimethyltaurate/VP Copolymer, Carbomer, Pentylene Glycol, Tromethamine, Ethylhexylglycerin, Sodium Benzoate, Phenoxyethanol.

DOSAGE AND ADMINISTRATION

• Sun Protection Measures

Spending time in the sun increases your risk of skin cancer and early skin aging.

To decrease this risk, regularly use a sunscreen with a broad spectrum SPF of 15 or higher and other sun protection measures including:

• Limit time in the sun, especially from 10 a.m. - 2 p.m.

• Wear long-sleeved shirts, pants, hats, and sunglasses

• Children under 6 months of age: Ask a doctor.

Warnings For external use only

Directions

• Apply generously 15 minutes before sun exposure

• Reapply at least every 2 hours

• Use a water resistant sunscreen if swimming or sweating

PACKAGE LABEL

Idealove

HydroGlow Daily Sunscreen SPF 50 BROAD SPECTRUM SPF 50 UVA & UVB

100 mL / 3.3 fl oz